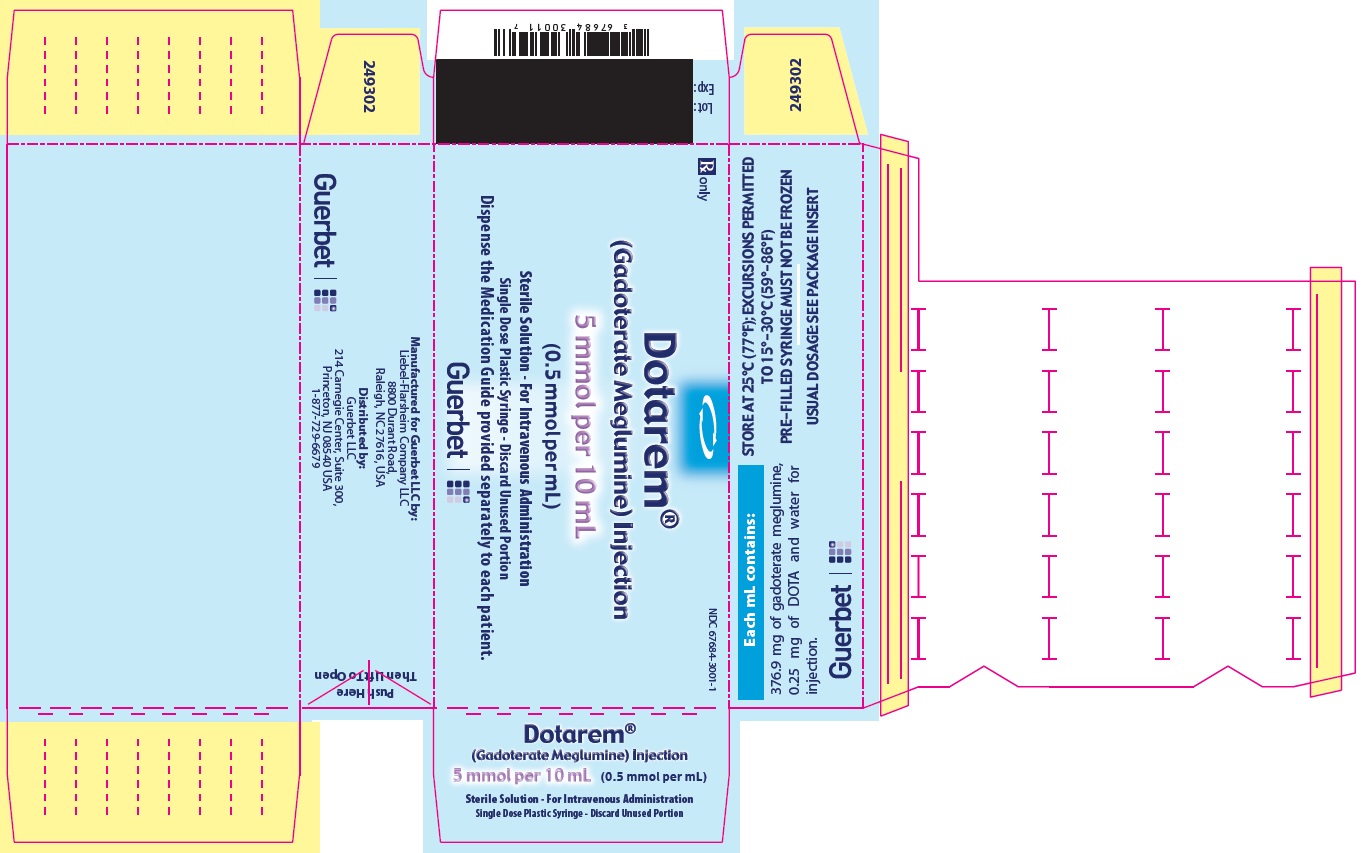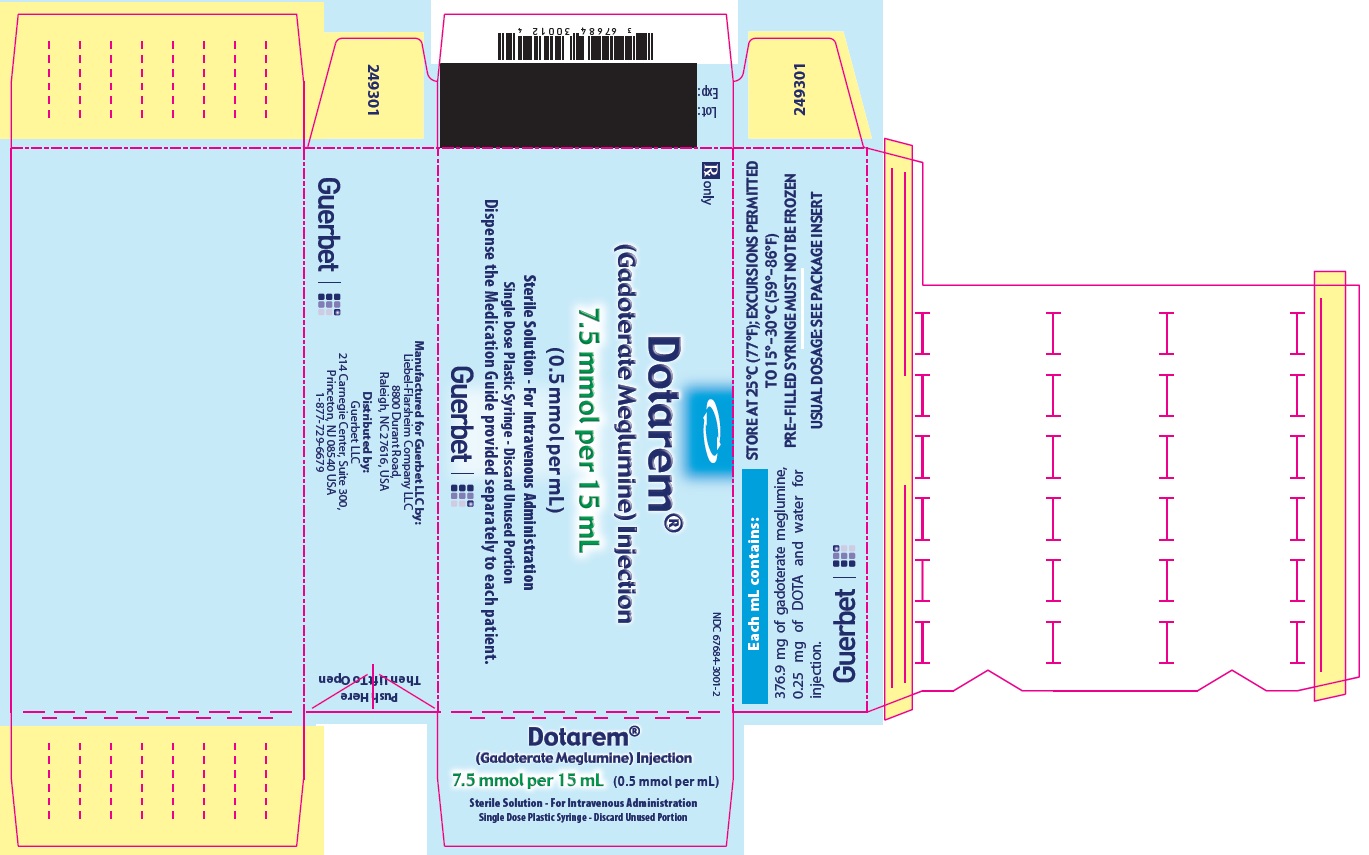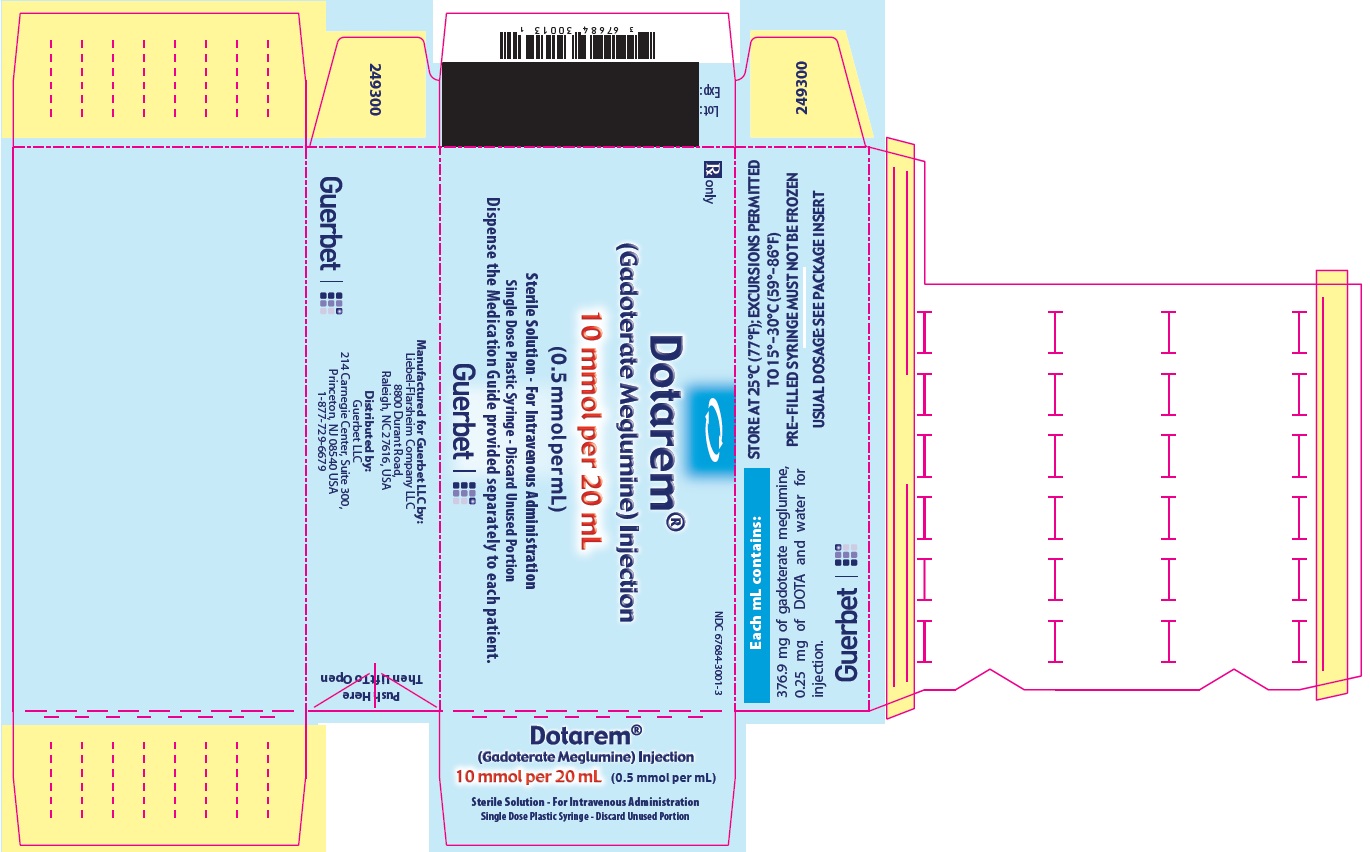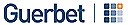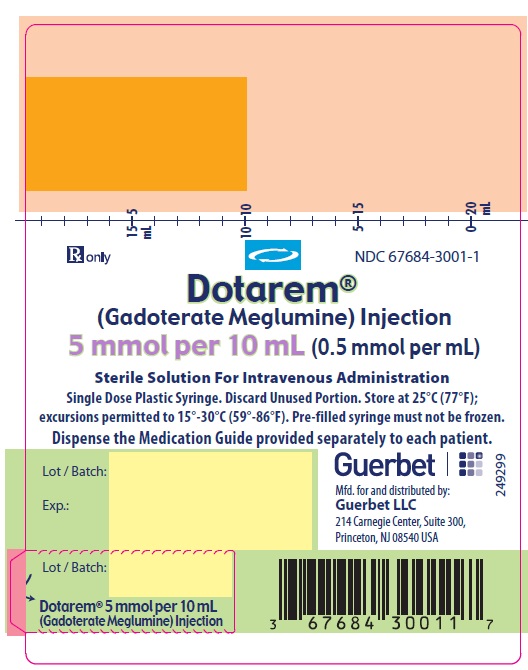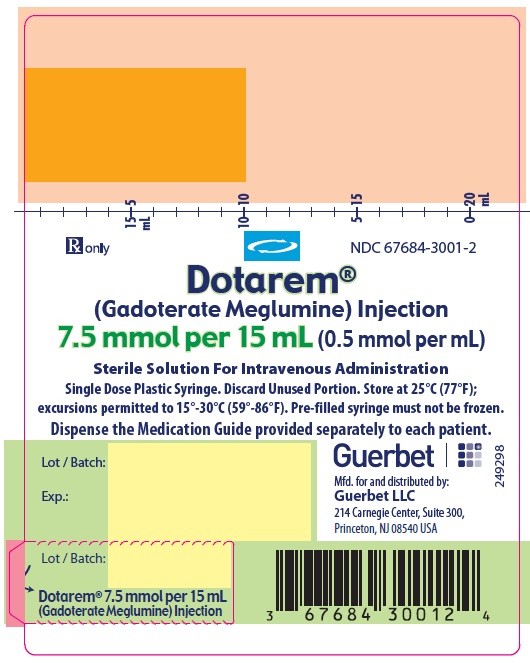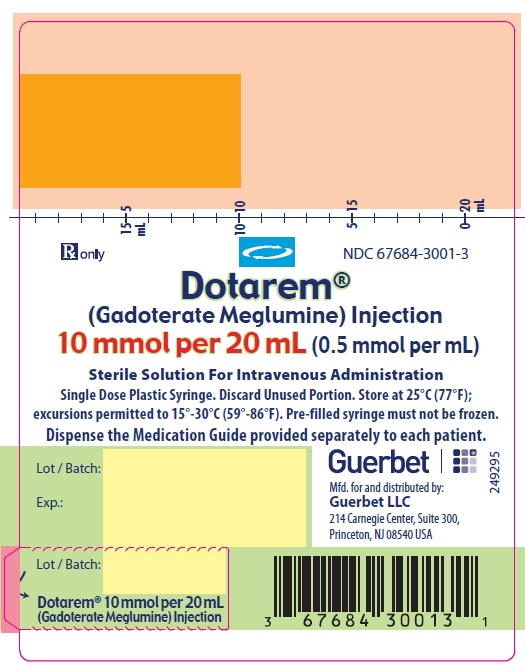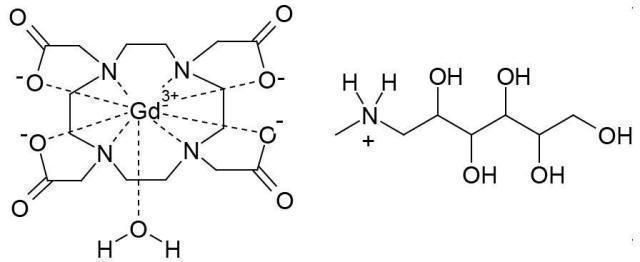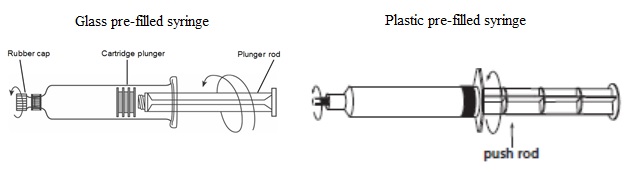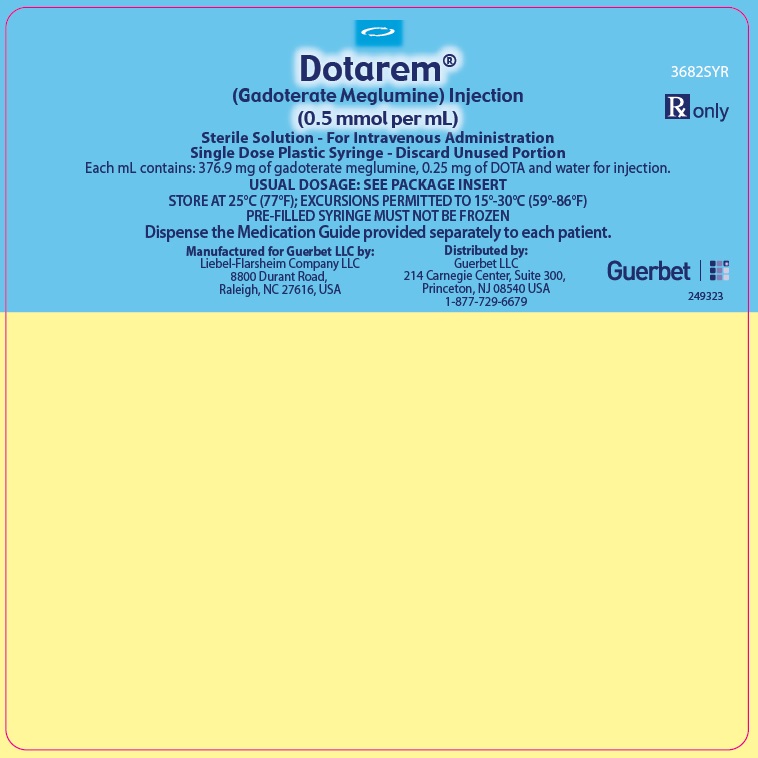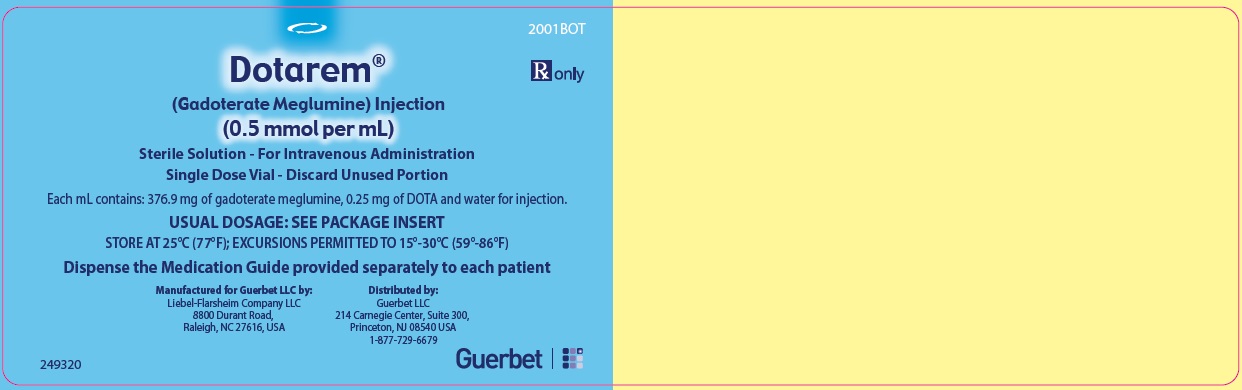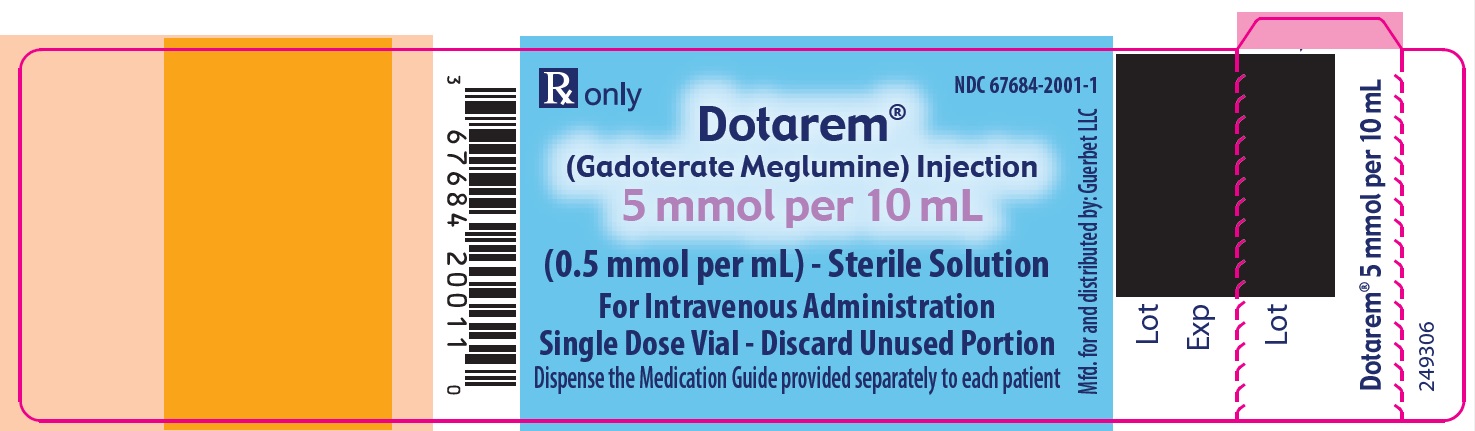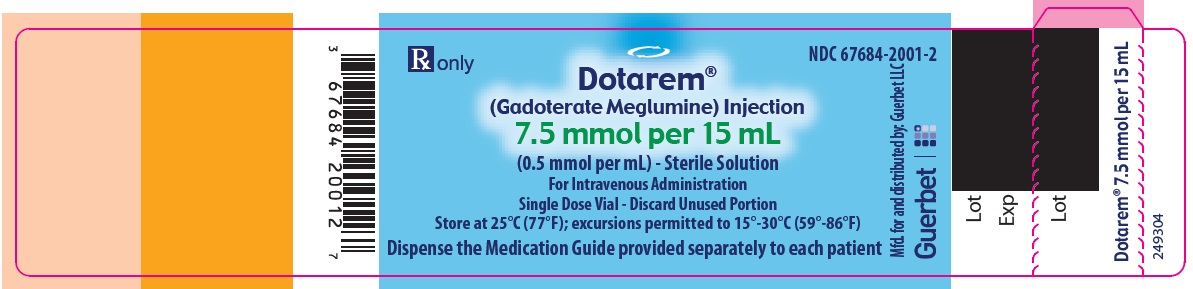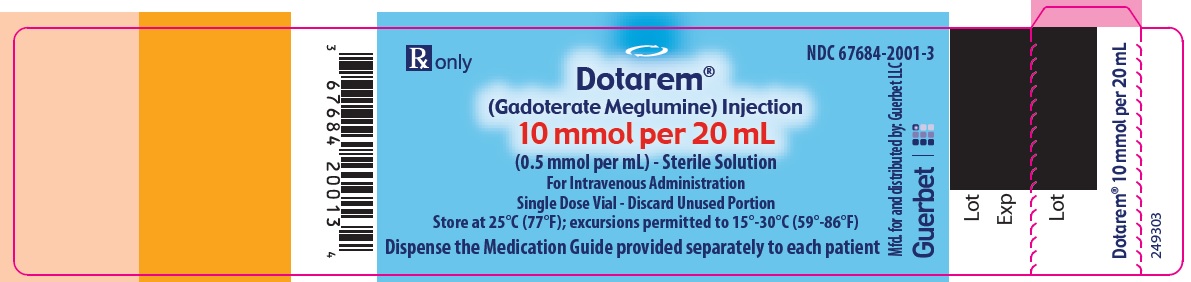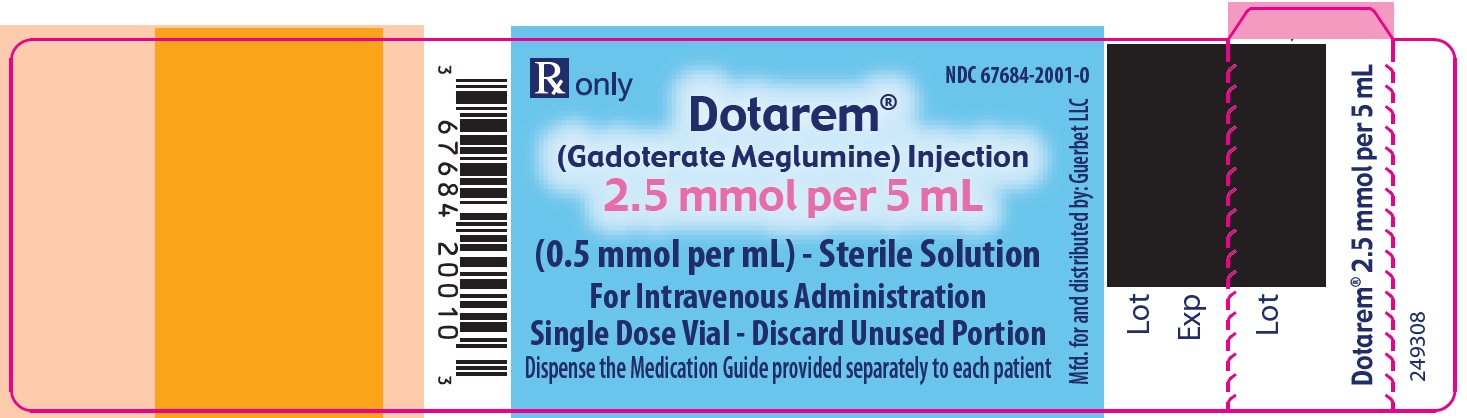 DRUG LABEL: DOTAREM
NDC: 67684-2000 | Form: INJECTION
Manufacturer: Guerbet LLC
Category: prescription | Type: HUMAN PRESCRIPTION DRUG LABEL
Date: 20250314

ACTIVE INGREDIENTS: GADOTERATE MEGLUMINE 376.9 mg/1 mL
INACTIVE INGREDIENTS: WATER 1 mL/1 mL

HIGHLIGHTS OF PRESCRIBING INFORMATION

These highlights do not include all the information needed to use DOTAREM safely and effectively. See full prescribing information for DOTAREM.
DOTAREM® (gadoterate meglumine) Injection for intravenous use
Initial U.S. Approval: 2013

WARNING: RISK ASSOCIATED WITH INTRATHECAL USE and NEPHROGENIC SYSTEMIC FIBROSIS

See full prescribing information for complete boxed warning

- Intrathecal administration of gadolinium-based contrast agents (GBCAs) can cause serious adverse reactions including death, coma, encephalopathy, and seizures. DOTAREM is not approved for intrathecal use. (5.1)
- GBCAs increase the risk for nephrogenic systemic fibrosis (NSF) among patients with impaired elimination of the drugs. Avoid use of DOTAREM in these patients unless the diagnostic information is essential and not available with non-contrasted MRI or other modalities. The risk for NSF appears highest among patients with:
  - Chronic, severe kidney disease (GFR < 30 mL/min/1.73 m^2), or
  - Acute kidney injury.

Screen patients for acute kidney injury and other conditions that may reduce renal function. For patients at risk for chronically reduced renal function (for example, age > 60 years, hypertension or diabetes), estimate the glomerular filtration rate (GFR) through laboratory testing (5.2).

1 INDICATIONS AND USAGE

DOTAREM is a gadolinium-based contrast agent indicated for intravenous use with magnetic resonance imaging (MRI) in brain (intracranial), spine and associated tissues in adult and pediatric patients (including term neonates) to detect and visualize areas with disruption of the blood brain barrier (BBB) and/or abnormal vascularity.

2 DOSAGE AND ADMINISTRATION

Adult and pediatric patients: The recommended dose of DOTAREM is 0.2 mL/kg (0.1 mmol/kg) body weight administered as an intravenous bolus injection at a flow rate of approximately 2 mL/second for adults and 1 - 2 mL/second for pediatric patients (including term neonates). The dose is delivered by manual or power injection.

3 DOSAGE FORMS AND STRENGTHS

DOTAREM Injection 0.5 mmol/mL contains 376.9 mg/mL of gadoterate meglumine and is available in vials and pre-filled syringes.

4 CONTRAINDICATIONS

Clinically important hypersensitivity reactions to DOTAREM.

5 WARNINGS AND PRECAUTIONS

- Hypersensitivity Reactions: Anaphylactoid/anaphylactic reactions with cardiovascular, respiratory or cutaneous manifestations, ranging from mild to severe, including death, have uncommonly occurred. Monitor patients closely for need of emergency cardiorespiratory support. (5.3)
- Gadolinium Retention: Gadolinium is retained for months or years in brain, bone, and other organs. (5.4)

6 ADVERSE REACTIONS

The most frequent (≥ 0.2%) adverse reactions in clinical studies were nausea, headache, injection site pain, injection site coldness, and rash. (6.1)

To report SUSPECTED ADVERSE REACTIONS, contact GUERBET LLC at 1-877-729-6679 or FDA at 1-800-FDA-1088 or www.fda.gov/medwatch.

8 USE IN SPECIFIC POPULATIONS

Pregnancy: Use only if imaging is essential during pregnancy and cannot be delayed. (8.1)

FULL PRESCRIBING INFORMATION

WARNING: RISK ASSOCIATED WITH INTRATHECAL USE and NEPHROGENIC SYSTEMIC FIBROSIS

Risk Associated with Intrathecal Use

Intrathecal administration of gadolinium-based contrast agents (GBCAs) can cause serious adverse
reactions including death, coma, encephalopathy, and seizures. DOTAREM is not approved for
intrathecal use [see Warnings and Precautions (5.1)].

Nephrogenic Systemic Fibrosis

GBCAs increase the risk for nephrogenic systemic fibrosis (NSF) among patients with impaired elimination of the drugs. Avoid use of DOTAREM in these patients unless the diagnostic information is essential and not available with non-contrasted MRI or other modalities. NSF may result in fatal or debilitating fibrosis affecting the skin, muscle and internal organs.

The risk for NSF appears highest among patients with:

- Chronic, severe kidney disease (GFR < 30 mL/min/1.73 m ^2), or
- Acute kidney injury.

Screen patients for acute kidney injury and other conditions that may reduce renal function. For patients at risk for chronically reduced renal function (e.g. age > 60 years, hypertension, diabetes), estimate the glomerular filtration rate (GFR) through laboratory testing (5.1).

For patients at highest risk for NSF, do not exceed the recommended DOTAREM dose and allow a sufficient period of time for elimination of the drug from the body prior to any re-administration [see Warnings and Precautions (5.2)] .

1 INDICATIONS AND USAGE

DOTAREM is a gadolinium-based contrast agent indicated for intravenous use with magnetic resonance imaging (MRI) in brain (intracranial), spine and associated tissues in adult and pediatric patients (including term neonates) to detect and visualize areas with disruption of the blood brain barrier (BBB) and/or abnormal vascularity.

2 DOSAGE AND ADMINISTRATION

2.1 Dosing Guidelines

For adult and pediatric patients (including term neonates), the recommended dose of DOTAREM is 0.2 mL/kg (0.1 mmol/kg) body weight administered as an intravenous bolus injection, manually or by power injector, at a flow rate of approximately 2 mL/second for adults and 1 - 2 mL/second for pediatric patients. Table 1 provides weight-adjusted dose volumes.

Table 1: Volumes of DOTAREM Injection by Body Weight
Body Weight |  | Volume
Pounds (lb) | Kilograms (kg) | Milliliters (mL)
5.5 | 2.5 | 0.5
11 | 5 | 1
22 | 10 | 2
44 | 20 | 4
66 | 30 | 6
88 | 40 | 8
110 | 50 | 10
132 | 60 | 12
154 | 70 | 14
176 | 80 | 16
198 | 90 | 18
220 | 100 | 20
242 | 110 | 22
264 | 120 | 24
286 | 130 | 26
308 | 140 | 28
330 | 150 | 30

To ensure complete injection of DOTAREM the injection may be followed by normal saline flush. Contrast MRI can begin immediately following DOTAREM injection.

2.2 Drug Handling

- Visually inspect DOTAREM for particulate matter prior to administration. Do not use the solution if particulate matter is present or if the container appears damaged. DOTAREM should be a clear, colorless to yellow solution.
- Do not mix with other drugs or parenteral nutrition.
- Discard any unused portions of the drug.

Directions for Use of the DOTAREM (gadoterate meglumine) Injection

Glass vial:

Aseptically draw up the contrast medium into a disposable syringe and use immediately.

Glass or plastic pre-filled syringe:

1) Holding the syringe barrel firmly, screw the threaded tip of the plunger rod clockwise into the cartridge plunger.

- For glass pre-filled syringe: Push forward a few millimeters to break any friction between the cartridge plunger and syringe barrel.
- For plastic pre-filled syringe: After screwing the push rod into the syringe cartridge plunger, turn the push rod clockwise an additional ½ turn so that the cartridge plunger rotates freely.

2) Holding the syringe vertically so the rubber cap is pointed upward, aseptically remove the rubber cap from the tip of the syringe and attach either a sterile, disposable needle or compatible needleless luer lock tubing set using a push-twist action. At this point, the tubing set is not attached to a patient’s intravenous connection.

- If using a needleless luer lock tubing set, check the connection between the syringe and the tubing as the fluid flows. Ensure that the connection is successful before administration of DOTAREM Injection.
- If using a needle, hold the syringe vertically and push plunger forward until all of the air is evacuated and fluid either appears at the tip of the needle or the tubing is filled. Following the usual venous blood aspiration procedure, complete the DOTAREM injection.

3) To ensure complete delivery of the contrast medium, the injection may be followed by a normal saline flush.

4) Properly dispose of the syringe and any other materials used.

3 DOSAGE FORMS AND STRENGTHS

DOTAREM 0.5 mmol/mL is a sterile, clear, colorless to yellow, aqueous solution for intravenous injection containing 376.9 mg/mL gadoterate meglumine and is available in vials and pre-filled syringes.

4 CONTRAINDICATIONS

History of clinically important hypersensitivity reactions to DOTAREM [see Warnings and Precautions (5.2)] .

5 WARNINGS AND PRECAUTIONS

5.1 Risk Associated with Intrathecal Use

Intrathecal administration of GBCAs can cause serious adverse reactions including death, coma, encephalopathy, and seizures. The safety and effectiveness of DOTAREM have not been established with intrathecal use. DOTAREM is not approved for intrathecal use [see Dosage and Administration (2.1)].

5.2 Nephrogenic Systemic Fibrosis

GBCAs increase the risk for nephrogenic systemic fibrosis (NSF) among patients with impaired elimination of the drugs. Avoid use of DOTAREM among these patients unless the diagnostic information is essential and not available with non-contrast MRI or other modalities. The GBCA-associated NSF risk appears highest for patients with chronic, severe kidney disease (GFR < 30 mL/min/1.73 m ^2) as well as patients with acute kidney injury. The risk appears lower for patients with chronic, moderate kidney disease (GFR 30 - 59 mL/min/1.73 m ^2) and little, if any, for patients with chronic, mild kidney disease (GFR 60 - 89 mL/min/1.73 m ^2). NSF may result in fatal or debilitating fibrosis affecting the skin, muscle and internal organs. Report any diagnosis of NSF following DOTAREM administration to Guerbet LLC (1-877-729-6679) or FDA (1-800-FDA-1088 or www.fda.gov/medwatch).

Screen patients for acute kidney injury and other conditions that may reduce renal function. Features of acute kidney injury consist of rapid (over hours to days) and usually reversible decrease in kidney function, commonly in the setting of surgery, severe infection, injury or drug-induced kidney toxicity. Serum creatinine levels and estimated GFR may not reliably assess renal function in the setting of acute kidney injury. For patients at risk for chronically reduced renal function (e.g., age > 60 years, diabetes mellitus or chronic hypertension), estimate the GFR through laboratory testing.

The factors that may increase the risk for NSF are repeated or higher than recommended doses of a GBCA and the degree of renal impairment at the time of exposure. Record the specific GBCA and the dose administered to a patient. For patients at highest risk for NSF, do not exceed the recommended DOTAREM dose and allow a sufficient period of time for elimination of the drug prior to re-administration. For patients receiving hemodialysis, physicians may consider the prompt initiation of hemodialysis following the administration of a GBCA in order to enhance the contrast agent’s elimination. The usefulness of hemodialysis in the prevention of NSF is unknown [see Dosage and Administration (2) and Clinical Pharmacology (12)] .

5.3 Hypersensitivity Reactions

Anaphylactic and anaphylactoid reactions have been reported with DOTAREM, involving cardiovascular, respiratory, and/or cutaneous manifestations. Some patients experienced circulatory collapse and died. In most cases, initial symptoms occurred within minutes of DOTAREM administration and resolved with prompt emergency treatment [see Adverse Reactions (6)] .

- Before DOTAREM administration, assess all patients for any history of a reaction to contrast media, bronchial asthma and/or allergic disorders. These patients may have an increased risk for a hypersensitivity reaction to DOTAREM.
- Administer DOTAREM only in situations where trained personnel and therapies are promptly available for the treatment of hypersensitivity reactions, including personnel trained in resuscitation.
- During and following DOTAREM administration, observe patients for signs and symptoms of hypersensitivity reactions.

5.4 Gadolinium Retention

Gadolinium is retained for months or years in several organs. The highest concentrations (nanomoles per gram of tissue) have been identified in the bone, followed by other organs (e.g. brain, skin, kidney, liver and spleen). The duration of retention also varies by tissue and is longest in bone. Linear GBCAs cause more retention than macrocyclic GBCAs. At equivalent doses, gadolinium retention varies among the linear agents with Omniscan (gadodiamide) and Optimark (gadoversetamide) causing greater retention than other linear agents [Eovist (gadoxetate disodium), Magnevist (gadopentetate dimeglumine), MultiHance (gadobenate dimeglumine)]. Retention is lowest and similar among the macrocyclic GBCAs [Dotarem (gadoterate meglumine), Gadavist (gadobutrol), ProHance (gadoteridol)].

Consequences of gadolinium retention in the brain have not been established. Pathologic and clinical consequences of GBCA administration and retention in skin and other organs have been established in patients with impaired renal function [see Warnings and Precautions (5.2)] . There are rare reports of pathologic skin changes in patients with normal renal function. Adverse events involving multiple organ systems have been reported in patients with normal renal function without an established causal link to gadolinium retention [see Adverse Reactions (6.2)] .

While clinical consequences of gadolinium retention have not been established in patients with normal renal function, certain patients might be at higher risk. These include patients requiring multiple lifetime doses, pregnant and pediatric patients, and patients with inflammatory conditions. Consider the retention characteristics of the agent when choosing a GBCA for these patients. Minimize repetitive GBCA imaging studies, particularly closely spaced studies when possible.

5.5 Acute Kidney Injury

In patients with chronically reduced renal function, acute kidney injury requiring dialysis has occurred with the use of GBCAs. The risk of acute kidney injury may increase with increasing dose of the contrast agent; administer the lowest dose necessary for adequate imaging. Screen all patients for renal impairment by obtaining a history and/or laboratory tests. Consider follow-up renal function assessments for patients with a history of renal dysfunction.

5.6 Extravasation and Injection Site Reactions

Ensure catheter and venous patency before the injection of DOTAREM. Extravasation into tissues during DOTAREM administration may result in tissue irritation [see Nonclinical Toxicology (13.2)] .

6 ADVERSE REACTIONS

The following clinically significant adverse reactions are described elsewhere in the labeling: Nephrogenic systemic fibrosis [see Warnings and Precautions (5.2)] .

Hypersensitivity reactions [see Warnings and Precautions (5.3)].

Gadolinium Retention [see Warnings and Precautions (5.4)]

6.1 Clinical Trials Experience

Because clinical trials are conducted under widely varying conditions, adverse reaction rates observed in the clinical trials of a drug cannot be directly compared to rates in the clinical trials of another drug and may not reflect the rates observed in clinical practice.

The data described below reflect DOTAREM exposure in 2867 patients, representing 2682 adults and 185 pediatric patients. Overall, 55% of the patients were men. In clinical trials where ethnicity was recorded the ethnic distribution was 81% Caucasian, 11% Asian, 4% Black, and 4% others. The average age was 53 years (range from < 1 week to 97 years).

Overall, 4% of patients reported at least one adverse reaction, primarily occurring immediately or within 24 hours following DOTAREM administration. Most adverse reactions were mild or moderate in severity and transient in nature.

Table 2 lists adverse reactions that occurred in ≥ 0.2% patients who received DOTAREM.

Table 2: Adverse Reactions in Clinical Trials
Reaction | Rate (%); n=2867
Nausea | 0.6%
Headache | 0.4%
Injection Site Pain | 0.4%
Injection Site Coldness | 0.2%
Rash | 0.2%

Adverse reactions that occurred with a frequency < 0.2% in patients who received DOTAREM include: feeling cold, feeling hot, burning sensation, somnolence, pain, dizziness, dysgeusia, blood creatinine increased, hypotension, hypertension, asthenia, fatigue, injection site reactions (inflammation, extravasation, pruritus, swelling, warmth), paresthesia, pruritus, laryngeal discomfort, pain in extremity, vomiting, anxiety and palpitations.

Adverse Reactions in Pediatric Patients

During clinical trials, 185 pediatric patients (52 aged < 24 months, 33 aged 2 - 5 years, 57 aged 6 - 11 years and 43 aged 12 - 17 years) received DOTAREM. Overall, 7 pediatric patients (3.8%) reported at least one adverse reaction following DOTAREM administration. The most frequently reported adverse reaction was headache (1.1%). Most adverse events were mild in severity and transient in nature.

6.2 Postmarketing Experience

The following additional adverse reactions have been identified during postmarketing use of DOTAREM or other GBCAs. Because these reactions are reported voluntarily from a population of uncertain size, it is not always possible to reliably estimate their frequency or establish a causal relationship to drug exposure.

Table 3: Adverse Reactions in the Postmarketing Experience
System Organ Class | Adverse Reaction
Cardiac Disorders | bradycardia, tachycardia, arrhythmia
Immune System Disorders | hypersensitivity /anaphylactoid reactions including cardiac arrest, respiratory arrest, cyanosis, pharyngeal edema, laryngospasm, bronchospasm, angioedema, conjunctivitis, ocular hyperemia, eyelid edema, lacrimation increased, hyperhidrosis, urticaria
Nervous System Disorders | coma, convulsion, syncope, presyncope, parosmia, tremor
Musculoskeletal and Connective Tissue Disorders | muscle contracture, muscle weakness
Gastrointestinal Disorders | diarrhea, salivary hypersecretion, acute pancreatitis with onset within 48 hours after GBCA administration
General Disorders and Administration Site Conditions | malaise, fever; Adverse reactions with variable onset and duration have been reported after GBCA administration. These include fatigue, asthenia, pain syndromes, and heterogeneous clusters of symptoms in the neurological, cutaneous, and musculoskeletal systems.
Respiratory, Thoracic and Mediastinal Disorders | Acute respiratory distress syndrome, pulmonary edema
Skin and Subcutaneous Tissue Disorders | NSF, in patients whose reports were confounded by the receipt of other GBCAs or in situations where receipt of other GBCAs could not be ruled out.; No unconfounded cases of NSF have been reported with DOTAREM.; Gadolinium-associated plaques
Vascular Disorders | superficial phlebitis

7 DRUG INTERACTIONS

Gadoterate does not interfere with serum and plasma calcium measurements determined by colorimetric assays. Specific drug interaction studies with DOTAREM have not been conducted.

8 USE IN SPECIFIC POPULATIONS

8.1 Pregnancy

Risk Summary

GBCAs cross the human placenta and result in fetal exposure and gadolinium retention. The human data on the association between GBCAs and adverse fetal outcomes are limited and inconclusive (see Data). In animal reproduction studies, there were no adverse developmental effects observed in rats or rabbits with intravenous administration of gadoterate meglumine during organogenesis at doses up to 16 and 10 times, respectively, the recommended human dose (see Data). Because of the potential risks of gadolinium to the fetus, use DOTAREM only if imaging is essential during pregnancy and cannot be delayed.

The estimated background risk of major birth defects and miscarriage for the indicated population(s) are unknown. All pregnancies have a background risk of birth defect, loss, or other adverse outcomes. In the U.S. general population, the estimated background risk of major birth defects and miscarriage in clinically recognized pregnancies is 2-4% and 15-20% respectively.

Data

Human Data

Contrast enhancement is visualized in the placenta and fetal tissues after maternal GBCA administration.

Cohort studies and case reports on exposure to GBCAs during pregnancy have not reported a clear association between GBCAs and adverse effects in the exposed neonates. However, a retrospective cohort study, comparing pregnant women who had a GBCA MRI to pregnant women who did not have an MRI, reported a higher occurrence of stillbirths and neonatal deaths in the group receiving GBCA MRI. Limitations of this study include a lack of comparison with non-contrast MRI and lack of information about the material indication for MRI. Overall, these data preclude a reliable evaluation of the potential risk of adverse fetal outcomes with the use of GBCAs in pregnancy.

Animal Data

Gadolinium Retention

GBCAs administered to pregnant non-human primates (0.1 mmol/kg on gestational days 85 and 135) result in measurable gadolinium concentration in the offspring in bone, brain, skin, liver, kidney, and spleen for at least 7 months. GBCAs administered to pregnant mice (2 mmol/kg daily on gestational days 16 through 19) result in measurable gadolinium concentrations in the pups in bone, brain, kidney, liver, blood, muscle, and spleen at one month postnatal age.

Reproductive Toxicology

Gadoterate meglumine was administered in intravenous doses of 0, 2, 4 and 10 mmol/kg/day [3, 7 and 16 times the recommended human dose (RHD) based on body surface area (BSA)) to female rats for 14 days before mating, throughout the mating period and until gestation day (GD) 17. Pregnant rabbits were administered gadoterate meglumine in intravenous doses levels of 0, 1, 3 and 7 mmol/kg/day (3, 10 and 23 times the RHD based on BSA) from GD6 to GD19. No effects on embryo-fetal development were observed at doses up to 10 mmol/kg/day in rats or 3 mmol/kg/day in rabbits. Maternal toxicity was observed in rats at 10 mmol/kg/day and in rabbits at 7 mmol/kg/day. This maternal toxicity was characterized in rats by a slightly lower litter size and gravid uterus weight compared to the control group, and in rabbits by a reduction in body weight and food consumption.

8.2 Lactation

Risk Summary
There are no data on the presence of gadoterate in human milk, the effects on the breastfed infant, or the effects on milk production. However, published lactation data on other GBCAs indicate that 0.01 to 0.04% of the maternal gadolinium dose is present in breast milk. Additionally, there is limited GBCA gastrointestinal absorption in the breast-fed infant. Gadoterate is present in goat milk (see Data). The developmental and health benefits of breastfeeding should be considered along with the mother’s clnical need for DOTAREM and any potential adverse effects on the breastfed infant from DOTAREM or from the underlying maternal condition.

Data
Nonclinical data demonstrate that gadoterate is detected in goat milk in amounts < 0.1% of the dose intravenously administered. Furthermore, in rats, absorption of gadoterate via the gastrointestinal tract is poor (1.2% of the administered dose was absorbed and eliminated in urine).

8.4 Pediatric Use

The safety and efficacy of DOTAREM at a single dose of 0.1 mmol/kg have been established in pediatric patients from birth (term neonates ≥ 37 weeks gestational age) to 17 years of age based on clinical data in 133 pediatric patients 2 years of age and older, and clinical data in 52 pediatric patients birth to less than 2 years of age that supported extrapolation from adult data [see Clinical Studies (14)] . Adverse reactions in pediatric patients were similar to those reported in adults [see Adverse Reactions (6.1)] . No dosage adjustment according to age is necessary in pediatric patients [See Dosage and Administration (2.1), Pharmacokinetics (12.3)] . The safety of DOTAREM has not been established in preterm neonates.

No cases of NSF associated with DOTAREM or any other GBCA have been identified in pediatric patients age 6 years and younger [see Warnings and Precautions (5.2)] . Normal estimated GFR (eGFR) is approximately 30 mL/minute/1.73m^2 at birth and increases to adult values by 2 years of age.

Juvenile Animal Data

Single and repeat-dose toxicity studies in neonatal and juvenile rats did not reveal findings suggestive of a specific risk for use in pediatric patients including term neonates and infants.

8.5 Geriatric Use

In clinical studies of DOTAREM, 900 patients were 65 years of age and over, and 304 patients were 75 years of age and over. No overall differences in safety or efficacy were observed between these subjects and younger subjects. In general, use of DOTAREM in elderly patients should be cautious, reflecting the greater frequency of impaired renal function and concomitant disease or other drug therapy. No age-related dosage adjustment is necessary.

8.6 Renal Impairment

No DOTAREM dosage adjustment is recommended for patients with renal impairment. Gadoterate can be removed from the body by hemodialysis [ see Warnings and Precautions (5.2) and Clinical Pharmacology (12.3) ].

10 OVERDOSAGE

DOTAREM administered to healthy volunteers and to adult patients at cumulative doses up to 0.3 mmol/kg was tolerated in a manner similar to lower doses. Adverse reactions to overdosage with DOTAREM have not been reported. Gadoterate meglumine can be removed from the body by hemodialysis [See Clinical Pharmacology (12.3)] .

11 DESCRIPTION

DOTAREM (gadoterate meglumine) is a paramagnetic macrocyclic ionic contrast agent administered for magnetic resonance imaging. The chemical name for gadoterate meglumine is D-glucitol, 1-deoxy-1-(methylamino)-,[1,4,7,10-tetraazacyclododecane-1,4,7,10-tetraaceto(4-)-.kappa.N1, .kappa.N4, .kappa.N7, .kappa.N10, .kappa.O1, .kappa.O4, .kappa.O7, .kappa.O10]gadolinate(1-)(1:1); it has a formula weight of 753.9 g/mol and empirical formula of C 23H 42O 13N 5Gd (anhydrous basis).

The structural formula of gadoterate meglumine in solution is as follows:

CAS Registry No. 92943-93-6

DOTAREM Injection is a sterile, nonpyrogenic, clear, colorless to yellow, aqueous solution of 0.5 mmol/mL of gadoterate meglumine. No preservative is added. Each mL of DOTAREM contains 376.9 mg of gadoterate meglumine, 0.25 mg of DOTA and water for injection. DOTAREM has a pH of 6.5 to 8.0.

The main physiochemical properties of DOTAREM are provided below:

Table 4: Physicochemical Properties
Parameter | Value
Density @ 20°C | 1.1753 g/cm ^3
Viscosity @ 20°C | 3.4 mPa.s
Viscosity @ 37°C | 2.4 mPa.s
Osmolality | 1350 mOsm/kg water

The thermodynamic stability constants for gadoterate (log K therm and log K cond at pH 7.4) are 25.6 and 19.3, respectively.

12 CLINICAL PHARMACOLOGY

12.1 Mechanism of Action

Gadoterate is a paramagnetic molecule that develops a magnetic moment when placed in a magnetic field. The magnetic moment enhances the relaxation rates of water protons in its vicinity, leading to an increase in signal intensity (brightness) of tissues.

In magnetic resonance imaging (MRI), visualization of normal and pathological tissue depends in part on variations in the radiofrequency signal intensity that occurs with:

1. differences in proton density
2. differences of the spin-lattice or longitudinal relaxation times (T1)
3. differences in the spin-spin or transverse relaxation time (T2)

When placed in a magnetic field, gadoterate shortens the T1 and T2 relaxation times in target tissues. At recommended doses, the effect is observed with greatest sensitivity in the T1-weighted sequences.

12.2 Pharmacodynamics

Gadoterate affects proton relaxation times and consequently the MR signal, and the contrast obtained is characterized by the relaxivity of the gadoterate molecule. The relaxivity values for gadoterate are similar across the spectrum of magnetic field strengths used in clinical MRI (0.2 - 1.5 T).

Disruption of the blood-brain barrier or abnormal vascularity allows distribution of gadoterate in lesions such as neoplasms, abscesses, and infarcts.

12.3 Pharmacokinetics

The pharmacokinetics of total gadolinium assessed up to 48 hours following an intravenously administered 0.1 mmol/kg dose of DOTAREM in healthy adult subjects demonstrated a mean elimination half-life (reported as mean ± SD) of about 1.4 ± 0.2 hr and 2.0 ± 0.7 hr in female and male subjects, respectively. Similar pharmacokinetic profile and elimination half-life values were observed after intravenous injection of 0.1 mmol/kg of DOTAREM followed 20 minutes later by a second injection of 0.2 mmol/kg (1.7 ± 0.3 hr and 1.9 ± 0.2 hr in female and male subjects, respectively).

Distribution

The volume of distribution at steady state of total gadolinium in healthy subjects is 179 ± 26 and 211 ± 35 mL/kg in female and male subjects respectively, roughly equivalent to that of extracellular water. Gadoterate does not undergo protein binding in vitro. The extent of blood cell partitioning of gadoterate is not known.

Following GBCA administration, gadolinium is present for months or years in brain, bone, skin and other organs [see Warnings and Precautions (5.4)].

Metabolism

Gadoterate is not known to be metabolized.

Elimination

Following a 0.1 mmol/kg dose of DOTAREM, total gadolinium is excreted primarily in the urine with 72.9 ± 17.0 % and 85.4 ± 9.7 % (mean ± SD) eliminated within 48 hours, in female and male subjects, respectively. Similar values were achieved after a cumulative dose of 0.3 mmol/kg (0.1 + 0.2 mmol/kg, 20 minutes later), with 85.5 ± 13.2 % and 92.0 ± 12.0 % recovered in urine within 48 hrs in female and male subjects respectively.

In healthy subjects, the renal and total clearance rates of total gadolinium are comparable (1.27 ± 0.32 and 1.74 ± 0.12 mL/min/kg in females; and 1.40 ± 0.31 and 1.64 ± 0.35 mL/min/kg in males, respectively) indicating that the drug is primarily cleared through the kidneys. Within the studied dose range (0.1 to 0.3 mmol/kg), the kinetics of total gadolinium appear to be linear.

Special Populations

Renal Impairment

A single intravenous dose of 0.1 mmol/kg of DOTAREM was administered to 8 patients (5 men and 3 women) with impaired renal function (mean serum creatinine of 498 ± 98 µmol/L in the 10 - 30 mL/min creatinine clearance group and 192 ± 62 µmol/L in the 30 - 60 mL/min creatinine clearance group). Renal impairment delayed the elimination of total gadolinium. Total clearance decreased as a function of the degree of renal impairment. The distribution volume was unaffected by the severity of renal impairment (Table 5). No changes in renal function test parameters were observed after DOTAREM injection. The mean cumulative urinary excretion of total gadolinium was approximately 76.9 ± 4.5% in 48 hrs in patients with moderate renal impairment, 68.4 ± 3.5% in 72 hrs in patients with severe renal impairment and 93.3 ± 4.7% in 24 hrs for subjects with normal renal function.

Table 5: Pharmacokinetic Profile of Total Gadolinium in Normal and Renally Impaired Patients
Population | Elimination Half-life; (hr) | Plasma Clearance; (L/h/kg) | Distribution Volume; (L/kg)
Healthy volunteers | 1.6 ± 0.2 | 0.10 ± 0.01 | 0.246 ± 0.03
Patients with moderate renal impairment | 5.1 ± 1.0 | 0.036 ± 0.007 | 0.236 ± 0.01
Patients with severe renal impairment | 13.9 ± 1.2 | 0.012 ± 0.001 | 0.234 ± 0.01

Gadoterate was shown to be dialyzable after an IV injection of DOTAREM in 10 patients with end-stage renal failure who required hemodialysis treatment. Gd serum concentration decreased over time by 88%, 93% and 97% at 0.5 hr, 1.5 hr, and 4 hrs after start of dialysis, respectively. A second and third hemodialysis session further removed Gd. After the third dialysis, Gd serum concentration decreased by 99.7%.

Pediatric population
The pharmacokinetics of gadoterate in pediatric patients receiving DOTAREM aged birth (term neonates) to 23 months, was investigated in an open label, multicenter study, using a population pharmacokinetics approach. A total of 45 subjects (22 males, 23 females) received a single intravenous dose of DOTAREM 0.1 mmol/kg (0.2 mL/kg). The age ranged from less than one week to 23.8 months (mean 9.9 months) and body weight ranged from 3 to 15 kg (mean 8.1 kg). Individual level of renal maturity in the study population, as expressed by eGFR ranged between 52 and 281 mL/min/1.73 m ^2 and 11 patients had an eGFR below 100 mL/min/1.73 m ^2 (range 52 to 95 mL/min/1.73 m ^2).

Gadoterate concentrations obtained up to 8 hours after DOTAREM administration were best fitted using a biphasic model with linear elimination from the intravascular space. The mean clearance adjusted to body weight was estimated at 0.16 ± 0.07 L/h/kg and increased with eGFR. The estimated mean elimination half-life was 1.47 ± 0.45 hr.

The body weight adjusted clearance of gadoterate after single intravenous injection of 0.1 mmol/kg of DOTAREM in pediatric subjects aged less than 2 years was similar to that observed in healthy adults.

13 NONCLINICAL TOXICOLOGY

13.1 Carcinogenesis, Mutagenesis, Impairment of Fertility

Long-term animal studies have not been performed to evaluate the carcinogenic potential of gadoterate meglumine.

Gadoterate meglumine did not demonstrate mutagenic potential in in vitro bacterial reverse mutation assays (Ames test) using Salmonella typhimurium, in an in vitro chromosome aberration assay in Chinese hamster ovary cells, in an in vitro gene mutation assay in Chinese hamster lung cells, nor in an in vivo mouse micronucleus assay.

No impairment of male or female fertility and reproductive performance was observed in rats after intravenous administration of gadoterate meglumine at the maximum tested dose of 10 mmol/kg/day (16 times the maximum human dose based on surface area), given during more than 9 weeks in males and more than 4 weeks in females. Sperm counts and sperm motility were not adversely affected by treatment with the drug.

13.2 Animal Toxicology and/or Pharmacology

Local intolerance reactions, including moderate irritation associated with infiltration of inflammatory cells were observed after perivenous injection in rabbits suggesting the possibility of local irritation if the contrast medium leaks around the veins in a clinical setting [see Warnings and Precautions (5.5)] .

Toxicity of gadoterate meglumine was evaluated in neonatal and juvenile (pre- and post-weaning) rats following a single or repeated intravenous administration at doses 1, 2, and 4 times the MHD based on BSA. Gadoterate meglumine was well tolerated at all dose levels tested and had no effect on growth, pre-weaning development, behavior and sexual maturation.

14 CLINICAL STUDIES

CNS Imaging

Efficacy and safety of DOTAREM were evaluated in a multi-center clinical trial (Study A) that enrolled 364 adult and 38 pediatric patients (aged ≥ 2 years) with known or suspected CNS lesions. Adults were randomized 2 to 1 to receive either DOTAREM or gadopentetate dimeglumine, each administered at a dose of 0.1 mmol/kg. All pediatric patients received DOTAREM, also at a dose of 0.1 mmol/kg. In the trial, patients first underwent a baseline (pre-contrast) MRI examination followed by the assigned GBCA administration and a post-contrast MR examination. The images (pre-contrast, post-contrast and “paired pre- and post-contrast”) were interpreted by three independent off-site readers blinded to clinical information. The primary efficacy analysis compared three patient-level visualization scores (paired images) to baseline MRI (pre-contrast images) for adults who received DOTAREM. The three primary visualization components were: contrast enhancement, border delineation and internal morphology. For each of these components there was a pre-defined scoring scale. Lesion counting (up to five per patient) was also reflected within each component’s patient-level visualization score.

Among the adult patients, 245 received DOTAREM and their data comprised the primary efficacy population. There were 114 (47%) men and 131 (53%) women with a mean age of 53 years (range 18 to 85 years), the racial and ethnic representations were 84% Caucasian, 11% Asian, 4% Black, and 1% other.

Table 6 displays a comparison of paired images (pre-and post-contrast) to pre-contrast images with respect to the proportion of patients who had paired image scores that were greater “better”, or same/worse “not better” than the pre-contrast scores and with respect to the difference in the mean patient level visualization score. Across the three readers 56% to 94% of patients had improved lesion visualization for paired images compared to pre-contrast images. DOTAREM provided a statistically significant improvement for all three primary visualization components. More lesions were seen on the paired images than the pre-contrast images.

Table 6: Study A. Improvement in Patient-level Lesion Visualization Scores, Paired versus Pre-contrast Images (a)
Lesion Scores | Reader 1 | Reader 2 | Reader 3
Lesion Scores | n = 231 | n = 232 | n = 237
Border Delineation
Better | 195 (84%) | 215 (93%) | 132 (56%)
Not Better | 28 (12%) | 7 (3%) | 88 (37%)
Missing | 8 (4%) | 10 (4%) | 17 (7%)
Difference in Mean Score (b) | 2.26 * | 2.89 * | 1.17 *
Internal Morphology
Better | 218 (94%) | 214 (93%) | 187 (79%)
Not Better | 5 (2%) | 8 (3%) | 33 (14%)
Missing | 8 (4%) | 10 (4%) | 17 (7%)
Difference in Mean Score (b) | 2.74 * | 2.75 * | 1.54 *
Contrast Enhancement
Better | 208 (90%) | 216 (93%) | 208 (88%)
Not Better | 15 (6%) | 6 (3%) | 12 (5%)
Missing | 8 (4%) | 10 (4%) | 17 (7%)
Difference in Mean Score (b) | 3.09 * | 3.69 * | 2.92 *

(a) Better: number of patients with paired (pre-and post-contrast) score greater than the pre-contrast score
Not better: number of patients with paired score same as or worse than the pre-contrast score
Missing: number of patients with missing score
(b) Difference = paired mean score minus pre-contrast mean score
*Statistically significant improvement by paired t-test

In secondary analyses, post-contrast images were improved in comparison to pre-contrast images. DOTAREM lesion visualization scores were similar to those for gadopentetate dimeglumine. DOTAREM imaging results in the pediatric patients were also similar to those seen in adults.

In a second clinical trial (Study B), MR images were reread from 150 adult patients with known CNS lesions who had participated in previously conducted clinical trial. DOTAREM administration and image interpretation was performed in the same manner as in Study A. Similar to Study A, this trial also demonstrated improved lesion visualization with DOTAREM.

CNS Imaging in the Sub-population of Pediatric Patients <2 years old

A non-randomized study (Study C) with 28 pediatric patients under 2 years of age who were referred for contrast MRI of the CNS supported extrapolation of CNS efficacy findings from adults and older children. CNS lesions were identified in 16 of these 28 patients on paired pre- and post-contrast images compared to 15 patients on pre-contrast images alone. In the 16 patients who had identifiable lesions, the scores for the co-endpoints of lesion visualization were improved for at least one lesion on paired pre- and post-contrast images compared to pre-contrast images in 8 out of 16 (50%) patients for lesion border delineation, 8 out of 16 (50%) patients for lesion internal morphology, and 14 out of 16 (88%) patients for lesion contrast enhancement.

16 HOW SUPPLIED/STORAGE AND HANDLING

DOTAREM Injection is a clear, colorless to yellow solution containing 0.5 mmol/mL of gadoterate meglumine. It is supplied in vials and prefilled syringes.

- DOTAREM Injection is supplied in 10 mL vials containing 5 mL or 10 mL of solution, in 20 mL vials containing 15 mL or 20 mL of solution.

Each single dose vial is closed with a rubber stopper and sealed with an aluminum cap and the contents are sterile. Vials are individually packaged in a shrink wrapped package of 10, in the following configurations:

5 mL in glass vial (NDC 67684-2000-0)

10 mL in glass vial (NDC 67684-2000-1)

15 mL in glass vial (NDC 67684-2000-2)

20 mL in glass vial (NDC 67684-2000-3)

Vials are also packaged in a box of 10, in the following configurations:

5 mL in glass vial (NDC 67684-2001-0)

10 mL in glass vial (NDC 67684-2001-1)

15 mL in glass vial (NDC 67684-2001-2)

20 mL in glass vial (NDC 67684-2001-3)

- DOTAREM Injection is supplied in 20 mL plastic pre-filled syringes containing 10 mL, 15 mL or 20 mL of solution

Each syringe is sealed with rubber closures and the contents are sterile. Syringes, including plunger rod, are packaged in a box of 10, in the following configurations:

10 mL in plastic pre-filled syringe (NDC 67684-3001-1)
15 mL in plastic pre-filled syringe (NDC 67684-3001-2)
20 mL in plastic pre-filled syringe (NDC 67684-3001-3)

Storage

Store at 25°C (77°F); excursions permitted to 15°C to 30°C (59°F to 86°F) [see USP, Controlled Room Temperature (CRT)].

Pre-filled syringes must not be frozen. Frozen syringes should be discarded.

Should solidification occur in the vial because of exposure to the cold, bring DOTAREM to room temperature before use. If allowed to stand at room temperature for a minimum of 90 minutes, DOTAREM should return to a clear, colorless to yellow solution. Before use, examine the product to assure that all solids are dissolved and that the container and closure have not been damaged. Discard the vial if solids persist.

17 PATIENT COUNSELING INFORMATION

• Advise the patient to read the FDA-approved patient labeling (Medication Guide)

17.1 Nephrogenic Systemic Fibrosis

Instruct patients to inform their healthcare provider if they:

1. have a history of kidney disease, or
2. have recently received a GBCA.

GBCAs increase the risk for NSF among patients with impaired elimination of the drugs. To counsel patients at risk for NSF:

- Describe the clinical manifestations of NSF.
- Describe procedures to screen for the detection of renal impairment.

Instruct the patients to contact their physician if they develop signs or symptoms of NSF following DOTAREM administration, such as burning, itching, swelling, scaling, hardening and tightening of the skin; red or dark patches on the skin; stiffness in joints with trouble moving, bending or straightening the arms, hands, legs or feet; pain in the hip bones or ribs; or muscle weakness.

17.2 Common Adverse Reactions

Inform patients that they may experience:

- Reactions along the venous injection site, such as mild and transient burning or pain or feeling of warmth or coldness at the injection site.
- Side effects of headache, nausea, abnormal taste and feeling hot.

17.3 General Precautions

- Pregnancy: Advise pregnant women of the potential risk of fetal exposure to gadoterate [see Use in Specific Populations (8.1)]
- Gadolinium Retention: Advise patients that gadolinium is retained for months or years in brain, bone, skin, and other organs in patients with normal renal function. The clinical consequences of retention are unknown. Retention depends on multiple factors and is greater following administration of linear GBCAs than following administration of macrocyclic GBCAs [see Warnings and Precautions (5.3)].

Rx Only

Guerbet LLC
214 Carnegie Center, Suite 300,
Princeteon, New Jersey 08540

Plastic pre-filled syringes manufactured by Liebel-Flarsheim Company LLC, USA for Guerbet

Vials manufactured by Recipharm, France and Liebel-Flarsheim Company LLC, USA for Guerbet

MEDICATION GUIDE

DOTAREM® (doh TAH rem)

(gadoterate meglumine)

Injection for intravenous use

What is the most important information I should know about DOTAREM?

- GBCAs like DOTAREM may cause serious side effects including death, coma, encephalopathy, and seizures when it is given intrathecally (injection given into the spinal canal). It is not known if DOTAREM is safe and effective with intrathecal use. DOTAREM is not approved for this use.
- DOTAREM contains a metal called gadolinium. Small amounts of gadolinium can stay in your body including the brain, bones, skin and other parts of your body for a long time (several months to years).
- It is not known how gadolinium may affect you, but so far, studies have not found harmful effects in patients with normal kidneys.
- Rarely patients have reported pains, tiredness, and skin, muscle or bone ailments for a long time, but these symptoms have not been directly linked to gadolinium.
- There are different GBCAs that can be used for your MRI exam. The amount of gadolinium that stays in the body is different for different gadolinium medicines. Gadolinium stays in the body more after Omniscan or Optimark than after Eovist, Magnevist or MultiHance. Gadolinium stays in the body the least after Dotarem, Gadavist or ProHance.
- People who get many doses of gadolinium medicines, women who are pregnant and young children may be at increased risk from gadolinium staying in the body.
- Some people with kidney problems who get gadolinium medicines can develop a condition with severe thickening of the skin, muscles and other organs in the body (nephrogenic systemic fibrosis). Your healthcare provider should screen you to see how well your kidneys are working before you receive DOTAREM.

What is DOTAREM?

- DOTAREM is a prescription medicine called a gadolinium-based contrast agent (GBCA). DOTAREM, like other GBCAs, is injected into your vein and used with a magnetic resonance imaging (MRI) scanner.
- An MRI exam with a GBCA, including DOTAREM, helps your doctor to see problems better than an MRI exam without a GBCA.
- Your doctor has reviewed your medical records and has determined that you would benefit from using a GBCA with your MRI exam.

Do not receive DOTAREM if you have had a severe allergic reaction to DOTAREM.

Before receiving DOTAREM, tell your healthcare provider about all your medical conditions, including if you:

- have had any MRI procedures in the past where you received a GBCA. Your healthcare provider may ask you for more information including the dates of these MRI procedures.
- are pregnant or plan to become pregnant. It is not known if DOTAREM can harm your unborn baby. Talk to your healthcare provider about the possible risks to an unborn baby if a GBCA such as DOTAREM is received during pregnancy.
- have kidney problems, diabetes, or high blood pressure.
- have had an allergic reaction to dyes (contrast agents) including GBCA

What are possible side effects of DOTAREM?

- See What is the most important information I should know about DOTAREM?
- Allergic reactions. DOTAREM can cause allergic reactions that can sometimes be serious. Your healthcare provider will monitor you closely for symptoms of an allergic reaction.

The most common side effects of DOTAREM include: nausea, headache, pain, or cold feeling at the injection site, and rash.
These are not all the possible side effects of DOTAREM.
Call your doctor for medical advice about side effects. You may report side effects to FDA at 1-800-FDA-1088.

General information about the safe and effective uses of DOTAREM.
Medicines are sometimes prescribed for purposes other than those listed in a Medication Guide. You can ask your healthcare provider for information about DOTAREM that is written for health professionals.

What are the ingredients in DOTAREM?

Active ingredient: gadoterate meglumine
Inactive ingredients: DOTA, water for injection
Manufactured by: Liebel-Flarsheim Company LLC (plastic pre-filled syringes and vials) and Recipharm (vials) for Guerbet
For more information, go to www.guerbet-us.com or call 1-877-729-6679.

This Medication Guide has been approved by the U.S. Food and Drug Administration. Rev. 3/2025